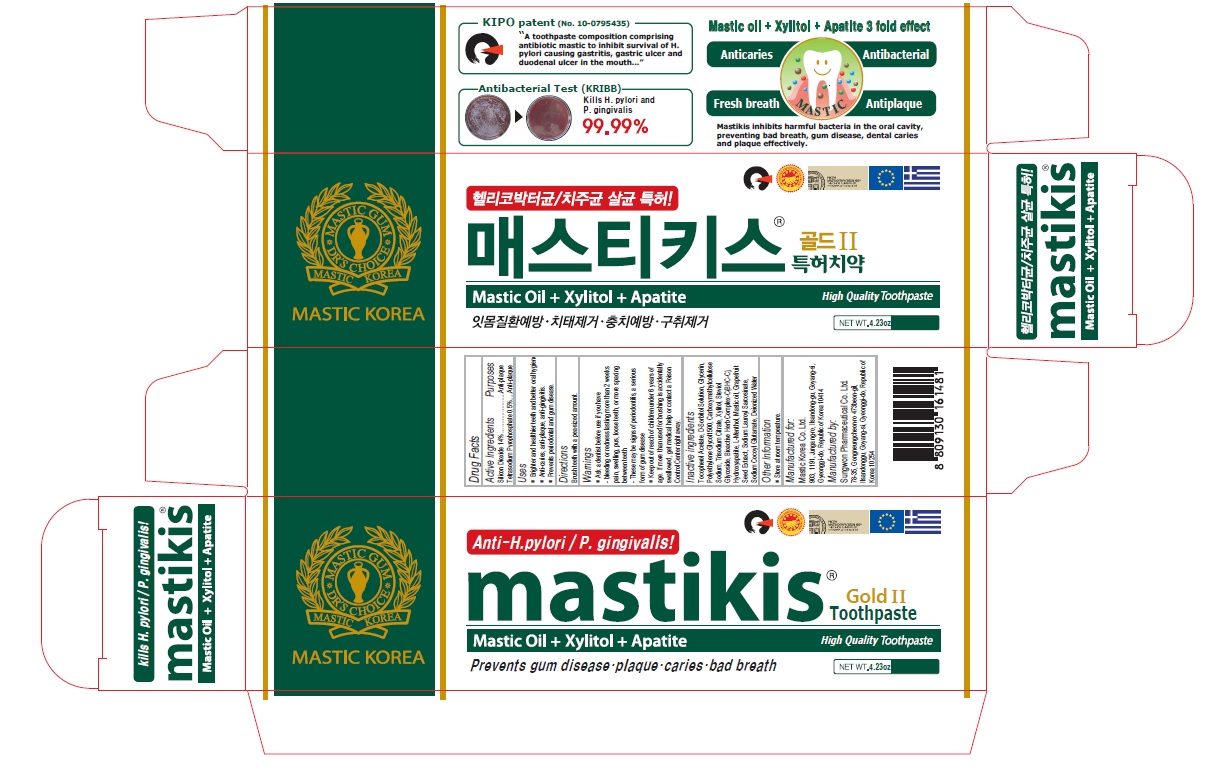 DRUG LABEL: Mastikis Gold II
NDC: 79814-002 | Form: PASTE, DENTIFRICE
Manufacturer: Mastic Korea.Co.Ltd
Category: otc | Type: HUMAN OTC DRUG LABEL
Date: 20200813

ACTIVE INGREDIENTS: SILICON DIOXIDE 14 g/100 g; SODIUM PYROPHOSPHATE 0.5 g/100 g
INACTIVE INGREDIENTS: .ALPHA.-TOCOPHEROL ACETATE; SORBITOL; GLYCERIN; POLYETHYLENE GLYCOL 1600; CARBOXYMETHYLCELLULOSE SODIUM, UNSPECIFIED; SODIUM CITRATE, UNSPECIFIED FORM; XYLITOL; STEVIOSIDE; LEVOMENTHOL; CITRUS PARADISI SEED; SODIUM LAUROYL SARCOSINATE; SODIUM COCOYL GLUTAMATE; WATER

79814-002_Mastikis Gold II toothpaste

ACTIVE INGREDIENT

Silicon Dioxide 14.0%
Tetrasodium Pyrophosphate 0.5%

INACTIVE INGREDIENT

Tocopherol Acetate, D-Sorbitol Solution, Glycerin, Polyethylene Glycol1500, Carboxymethylcellulose Sodium, Trisodium Citrate, Xylitol, Steviol Glycoside, Bioactive Herb Complex-C(BHC-C), Hydroxyapatite, L-Menthol, Mastic oil, Grapefruit Seed Extract, Sodium Lauroyl Sarcosinate, Sodium Cocoyl Glutamate, Deionized Water

Keep out of Reach of Children.

PURPOSE

Anti-plaque

WARNINGS

Ask a dentis before use if you have

- bleeding or redness lasting more than 2 weeks pain, welling, pus, loose teeth, or more spacing between teeth.

- These may be signs of periodontis, a serious from of gum disease

INDICATIONS AND USAGE

Brighter and healthier teeth and better oral hygine

Anti-caries, anti-plaque, anti-gingivitis

Prevents periodontal and gum disease

DOSAGE AND ADMINISTRATION

Brush teeth with a pea-sized amount